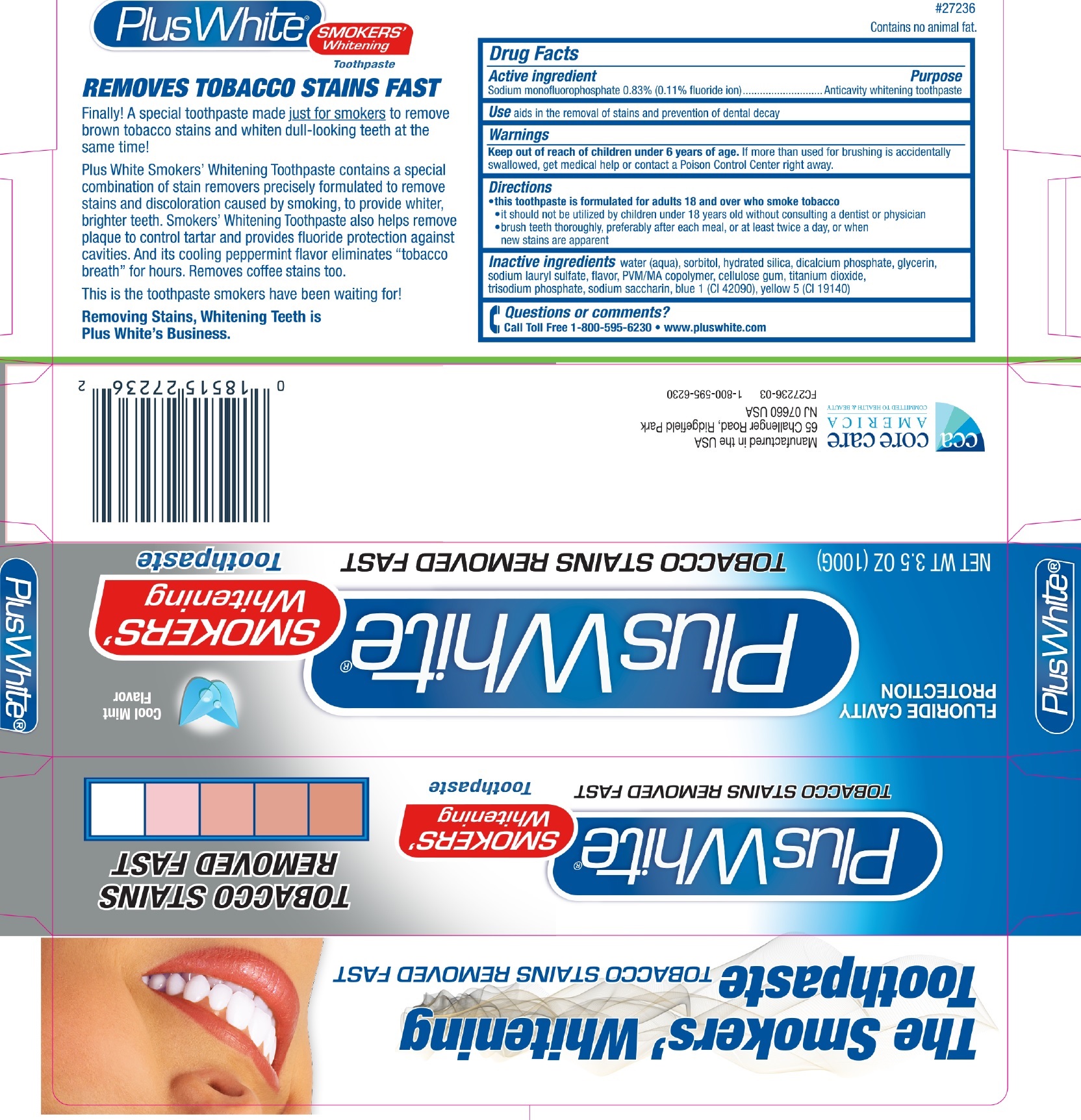 DRUG LABEL: Plus Plus White Smokers Whitening
NDC: 61543-7236 | Form: PASTE
Manufacturer: CCA Industries, Inc.
Category: otc | Type: HUMAN OTC DRUG LABEL
Date: 20200923

ACTIVE INGREDIENTS: SODIUM MONOFLUOROPHOSPHATE 1.5 mg/1 g
INACTIVE INGREDIENTS: WATER; SORBITOL; HYDRATED SILICA; ANHYDROUS DIBASIC CALCIUM PHOSPHATE; GLYCERIN; SODIUM LAURYL SULFATE; CARBOXYMETHYLCELLULOSE SODIUM; TITANIUM DIOXIDE; SACCHARIN SODIUM; FD&C BLUE NO. 1

Plus Plus White Smokers Whitening

Active ingredient

Sodium monofluorophosphate 0.83% (0.11% fluoride ion)

Purpose

Anticavity whitening toothpaste

Use

aids in the removal of stains and prevention of dental decay

Warnings

Keep out of reach of children under 6 years of age

If more than used for brushing is accidentally swallowed, get medical help or contact a Poison Control Center right away.

Directions

- this toothpaste is formulated for adults 18 and over who smoke tobacco
- it should not be utilized by children under 18 years old without consulting a dentist or physician
- brush teeth thoroughly, preferably after each meal, or at least twice a day, or when new stains are apparent

Inactive ingredients

water (aqua), sorbitol, hydrated silica, dicalcium phosphate, glycerin, sodium lauryl sulfate, flavor, PVM/MA copolymer, cellulose gum, titanium
dioxide, trisodium phosphate, sodium saccharin, blue 1 (CI 42090), yellow 5 (CI 19140).

Questions or comments?

Call Toll Free 1-800-595-6230 • www.pluswhite.com